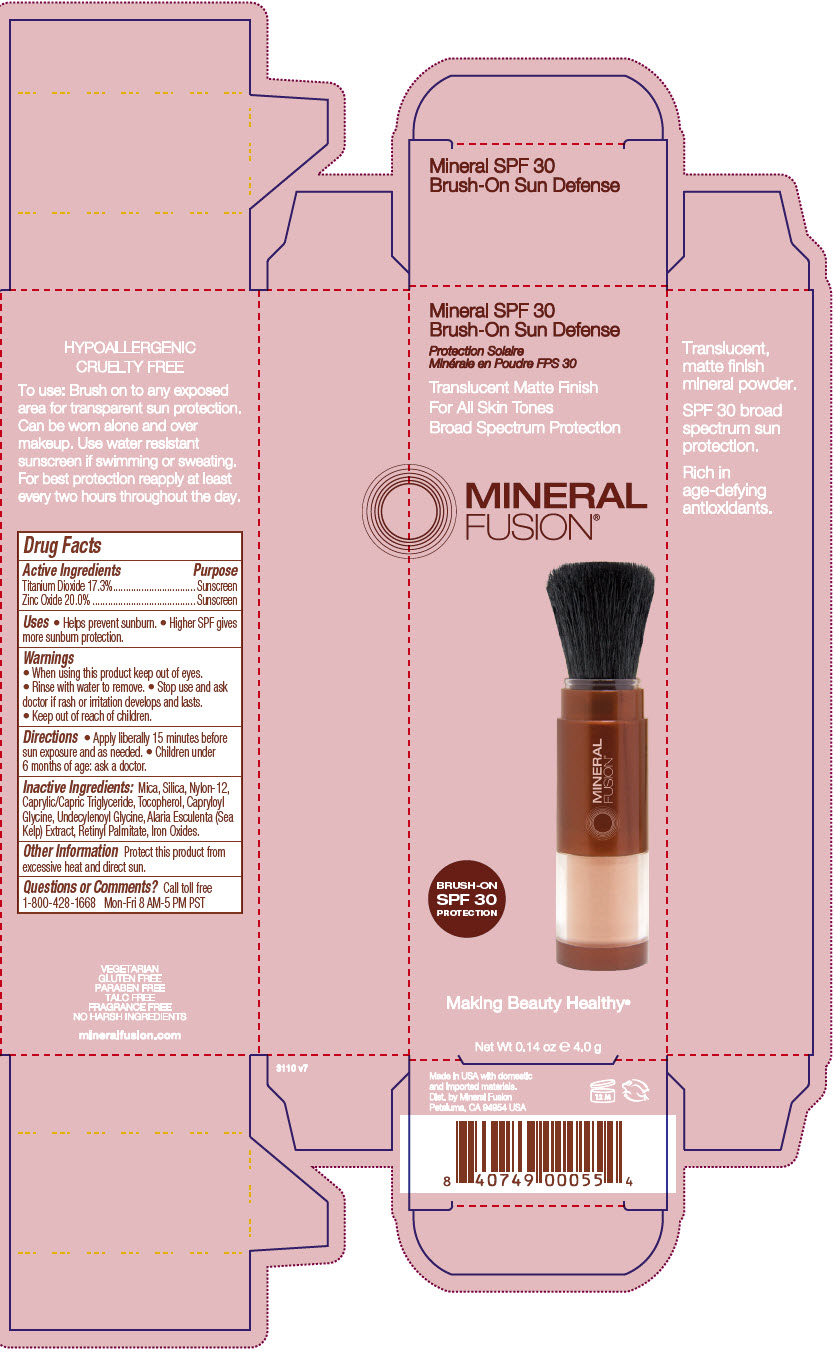 DRUG LABEL: Mineral SPF 30 Brush-On Sun Defense
NDC: 55789-1221 | Form: POWDER
Manufacturer: Mineral Fusion brands
Category: otc | Type: HUMAN OTC DRUG LABEL
Date: 20191231

ACTIVE INGREDIENTS: ZINC OXIDE 200 mg/1 g; TITANIUM DIOXIDE 173 mg/1 g
INACTIVE INGREDIENTS: MICA; SILICON DIOXIDE; NYLON-12; CAPRYLOYL GLYCINE; UNDECYLENOYL GLYCINE; ALARIA ESCULENTA; MEDIUM-CHAIN TRIGLYCERIDES; VITAMIN A PALMITATE; TOCOPHEROL; FERROSOFERRIC OXIDE; FERRIC OXIDE YELLOW; FERRIC OXIDE RED

Mineral SPF 30 Brush-On Sun Defense

Drug Facts

ACTIVE INGREDIENT

Active Ingredients | Purpose
Titanium Dioxide 17.3% | Sunscreen
Zinc Oxide 20.0% | Sunscreen

Uses

- Helps prevent sunburn.
- Higher SPF gives more sunburn protection.

Warnings

- When using this product keep out of eyes.
- Rinse with water to remove.
- Stop use and ask doctor if rash or irritation develops and lasts.

- Keep out of reach of children.

Directions

- Apply liberally 15 minutes before sun exposure and as needed.
- Children under 6 months of age: ask a doctor.

Inactive Ingredients

Mica, Silica, Nylon-12, Caprylic/Capric Triglyceride, Tocopherol, Capryloyl Glycine, Undecylenoyl Glycine, Alaria Esculenta (Sea Kelp) Extract, Retinyl Palmitate, Iron Oxides.

Other Information

Protect this product from excessive heat and direct sun.

Questions or Comments?

Call toll free 1-800-428-1668 Mon-Fri 8 AM-5 PM PST

Dist. by Mineral Fusion
Petaluma, CA 94954 USA

PRINCIPAL DISPLAY PANEL - 4 g Tube Carton

Mineral SPF 30
Brush-On Sun Defense

Translucent Matte Finish
For All Skin Tones
Broad Spectrum Protection

MINERAL
FUSION®

BRUSH-ON
SPF 30
PROTECTION

Making Beauty Healthy®

Net Wt 0.14 oz e 4.0 g